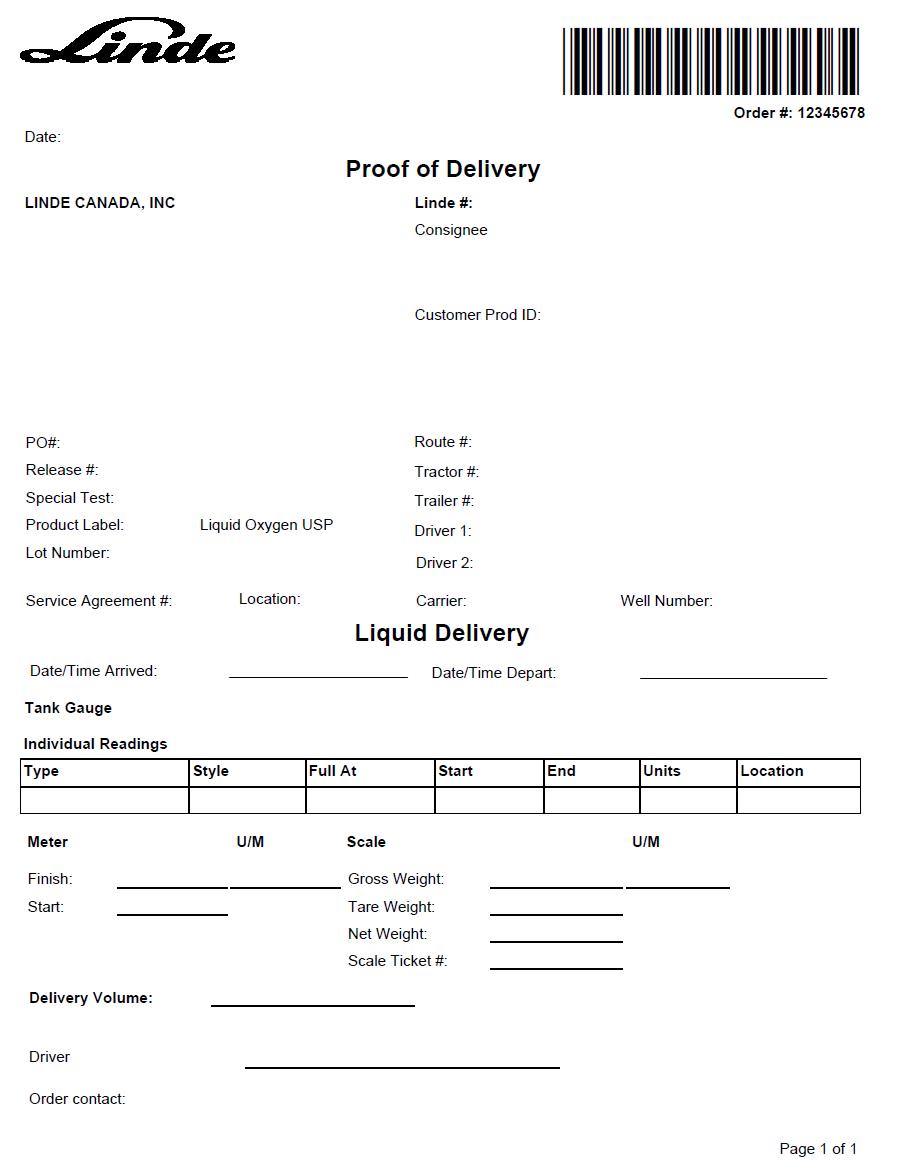 DRUG LABEL: Oxygen
NDC: 49479-722 | Form: GAS
Manufacturer: Linde Canada Inc.
Category: prescription | Type: HUMAN PRESCRIPTION DRUG LABEL
Date: 20251230

ACTIVE INGREDIENTS: OXYGEN 990 mL/1 L

Liquid Oxygen USP Canada